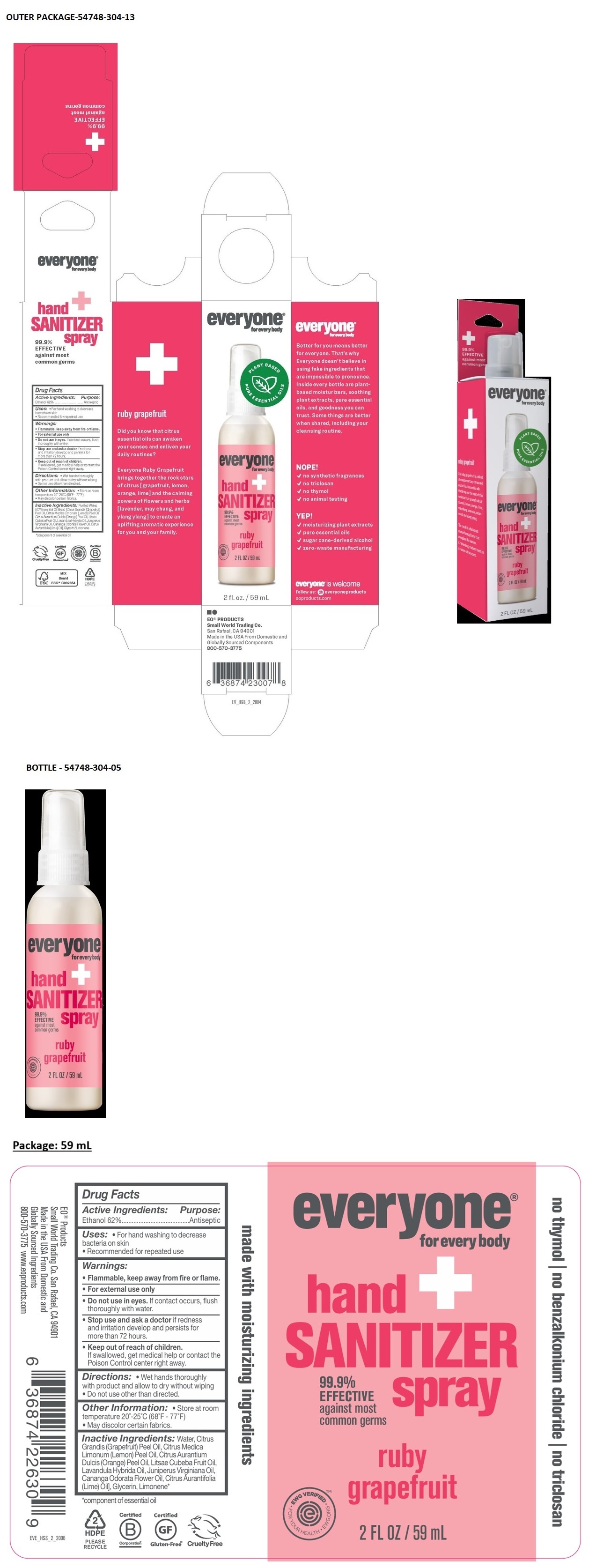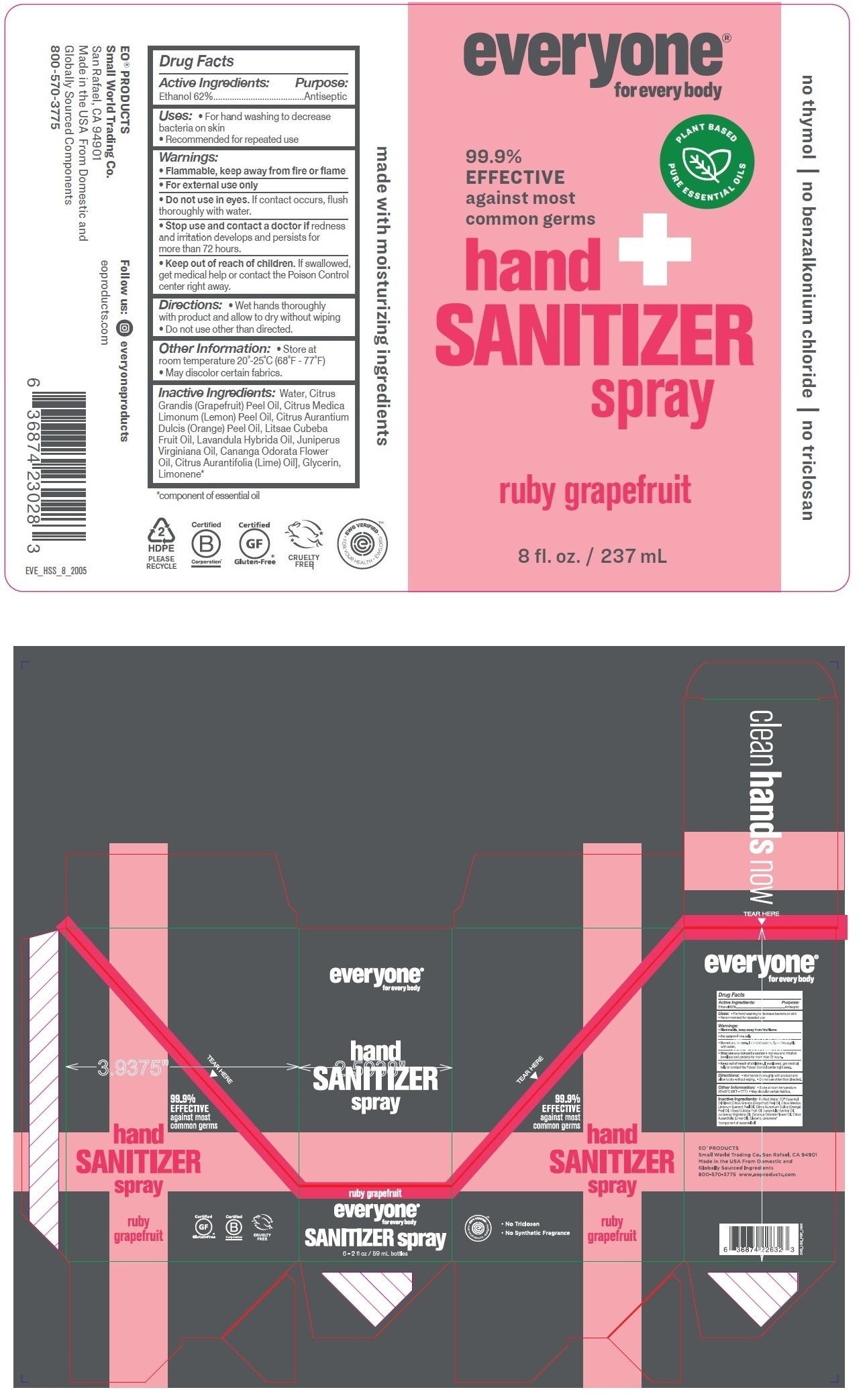 DRUG LABEL: Everyone Hand Sanitizer
NDC: 54748-304 | Form: SPRAY
Manufacturer: EO Products, LLC
Category: otc | Type: HUMAN OTC DRUG LABEL
Date: 20251127

ACTIVE INGREDIENTS: ALCOHOL 62 mL/100 mL
INACTIVE INGREDIENTS: WATER; CITRUS MAXIMA FRUIT RIND OIL; LEMON OIL, COLD PRESSED; ORANGE OIL, COLD PRESSED; LITSEA OIL; LAVANDIN OIL; JUNIPERUS VIRGINIANA OIL; YLANG-YLANG OIL; LIME OIL, COLD PRESSED; GLYCERIN; LIMONENE, (+)-

everyone® for everybody hand SANITIZER spray ruby grapefruit

Active Ingredients:

Ethanol 62%

Purpose:

Antiseptic

Uses:

• For hand washing to decrease bacteria on skin
• Recommended for repeated use

Warnings:

• Flammable, keep away from fire or flame.

• For external use only

• Do not use in eyes. If contact occurs, flush thoroughly with water.

• Stop use and ask a doctor if redness and irritation develops and persists for more than 72 hours.

• Keep out of reach of children.
If swallowed, get medical help or contact the Poison Control center right away.

Directions:

• Wet hands thoroughly with product and allow to dry without wiping
• Do not use other than directed.

Other Information:

• Store at room temperature 20˚-25˚C (68˚F - 77˚F)
• May discolor certain fabrics.

Inactive Ingredients:

Water, Citrus Grandis (Grapefruit) Peel Oil, Citrus Medica Limonum (Lemon) Peel Oil, Citrus Aurantium Dulcis (Orange) Peel Oil, Litsea Cubeba Fruit Oil, Lavandula Hybrida Oil, Juniperus Virginiana Oil, Cananga Odorata Flower Oil, Citrus Aurantifolia (Lime) Oil], Glycerin, Limonene*

*component of essential oil

99.9% EFFECTIVE against most common germs

no thymol | no benzalkonium chloride | no triclosan

EO® Products
Small World Trading Co. San Rafael, CA 94901
Made in the USA From Domestic and Globally Sourced Ingredients
800-570-3775 www.eoproducts.com

Certified Gluten-Free®

Cruelty Free

made with moisturizing ingredients